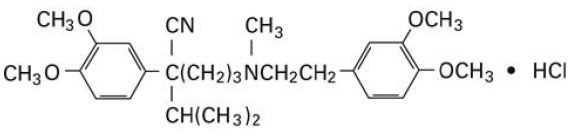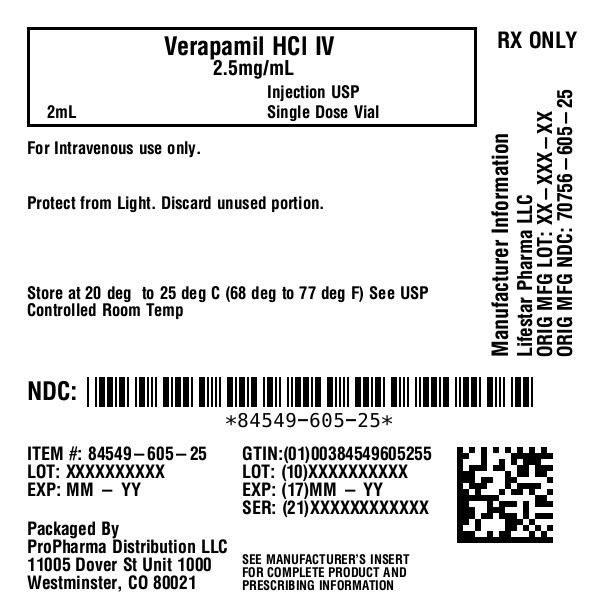 DRUG LABEL: verapamil hydrochloride
NDC: 84549-605 | Form: INJECTION, SOLUTION
Manufacturer: ProPharma Distribution
Category: prescription | Type: HUMAN PRESCRIPTION DRUG LABEL
Date: 20251218

ACTIVE INGREDIENTS: VERAPAMIL HYDROCHLORIDE 2.5 mg/1 mL
INACTIVE INGREDIENTS: HYDROCHLORIC ACID; SODIUM CHLORIDE; SODIUM HYDROXIDE; WATER

Verapamil Hydrochloride Injection, USP

Protect from light.

Rx only

DESCRIPTION

Verapamil hydrochloride is a calcium antagonist or slow-channel inhibitor. Verapamil Hydrochloride Injection, USP is a sterile, nonpyrogenic solution containing verapamil hydrochloride 2.5 mg/mL and sodium chloride 8.5 mg/mL in water for injection. The solution contains no bacteriostat or antimicrobial agent and is intended for single-dose intravenous administration. May contain hydrochloric acid and/or sodium hydroxide for pH adjustment; pH is 4.0 to 6.5.

The chemical name of Verapamil Hydrochloride, USP is benzeneacetonitrile, α-[3-[{2-(3,4-dimethoxyphenyl)ethyl} methylamino] propyl]-3,4-dimethoxy-α-(1-methylethyl) hydrochloride. Verapamil hydrochloride is a white or practically white crystalline powder. It is practically odorless and has a bitter taste. It is soluble in water; freely soluble in chloroform; sparingly soluble in alcohol; practically insoluble in ether. It has the following structural formula:

Molecular weight: 491.07

Molecular formula: C27H38N2O4• HCl

Verapamil hydrochloride is not chemically related to other antiarrhythmic drugs.

CLINICAL PHARMACOLOGY

Mechanism of Action:Verapamil inhibits the calcium ion (and possibly sodium ion) influx through slow channels into conductile and contractile myocardial cells and vascular smooth muscle cells. The antiarrhythmic effect of verapamil appears to be due to its effect on the slow channel in cells of the cardiac conduction system. The vasodilatory effect of verapamil appears to be due to its effect on blockade of calcium channels as well as α receptors.

In the isolated rabbit heart, concentrations of verapamil that markedly affect SA nodal fibers or fibers in the upper and middle regions of the AV node have very little effect on fibers in the lower AV node (NH region) and no effect on atrial action potentials or His bundle fibers.

Electrical activity in the SA and AV nodes depends, to a large degree, upon calcium influx through the slow channel. By inhibiting this influx, verapamil slows AV conduction and prolongs the effective refractory period within the AV node in a rate-related manner. This effect results in a reduction of the ventricular rate in patients with atrial flutter and/or atrial fibrillation and a rapid ventricular response.

By interrupting reentry at the AV node, verapamil can restore normal sinus rhythm in patients with paroxysmal supraventricular tachycardias (PSVT), including PSVT associated with Wolff-Parkinson-White syndrome.

Verapamil does not induce peripheral arterial spasm.

Verapamil has a local anesthetic action that is 1.6 times that of procaine on an equimolar basis. It is not known whether this action is important at the doses used in man.

Verapamil does not alter total serum calcium levels.

Hemodynamics:Verapamil reduces afterload and myocardial contractility. The commonly used intravenous doses of 5 to 10 mg verapamil hydrochloride produce transient, usually asymptomatic, reduction in normal systemic arterial pressure, systemic vascular resistance and contractility; left ventricular filling pressure is slightly increased. In most patients, including those with organic cardiac disease, the negative inotropic action of verapamil is countered by reduction of afterload, and cardiac index is usually not reduced. However, in patients with moderately severe to severe cardiac dysfunction (pulmonary wedge pressure above 20 mm Hg, ejection fraction less than 30%), acute worsening of heart failure may be seen. Peak therapeutic effects occur within 3 to 5 minutes after a bolus injection.

Pharmacokinetics:Intravenously administered verapamil hydrochloride has been shown to be rapidly metabolized. Following intravenous infusion in man, verapamil is eliminated bi-exponentially, with a rapid early distribution phase (half-life about 4 minutes) and a slower terminal elimination phase (half-life 2 to 5 hours). In healthy men, orally administered verapamil hydrochloride undergoes extensive metabolism in the liver, with 12 metabolites having been identified, most in only trace amounts. The major metabolites have been identified as various N- and O-dealkylated products of verapamil.

Approximately 70% of an administered dose is excreted in the urine and 16% more in the feces within 5 days. About 3% to 4% is excreted as unchanged drug.

Aging may affect the pharmacokinetics of verapamil given to hypertensive patients. Elimination half-life may be prolonged in the elderly.

INDICATIONS AND USAGE

Verapamil Hydrochloride Injection, USP is indicated for the following:

- Rapid conversion to sinus rhythm of paroxysmal supraventricular tachycardias, including those associated with accessory bypass tracts (Wolff-Parkinson-White [W-P-W] and Lown-Ganong- Levine [L-G-L] syndromes). When clinically advisable, appropriate vagal maneuvers (e.g., Valsalva maneuver) should be attempted prior to verapamil hydrochloride administration.
- Temporary control of rapid ventricular rate in atrial flutter or atrial fibrillation except when the atrial flutter and/or atrial fibrillation are associated with accessory bypass tracts (Wolff-Parkinson-White (W-P-W) and Lown-Ganong-Levine (L-G-L) syndromes).

In controlled studies in the United States, about 60% of patients with supraventricular tachycardia converted to normal sinus rhythm within 10 minutes after intravenous verapamil hydrochloride. Uncontrolled studies reported in the world literature describe a conversion rate of about 80%. About 70% of patients with atrial flutter and/or fibrillation with a faster ventricular rate respond with a decrease in ventricular rate of at least 20%. Conversion of atrial flutter or fibrillation to sinus rhythm is uncommon (about 10%) after verapamil hydrochloride and may reflect the spontaneous conversion rate, since the conversion rate after placebo was similar. Slowing of the ventricular rate in patients with atrial fibrillation/flutter lasts 30 to 60 minutes after a single injection.

Because a small fraction (<1%) of patients treated with verapamil hydrochloride respond with life-threatening adverse responses (rapid ventricular rate in atrial flutter/fibrillation, and anaccessory bypass tract, marked hypotension, or extreme bradycardia/asystole – see CONTRAINDICATIONSand WARNINGS), the initial use of verapamil hydrochloride injection should, if possible, be in a treatment setting with monitoring and resuscitation facilities, including D.C.-cardioversion capability (see ADVERSE REACTIONS, Suggested Treatment of Acute Cardiovascular Adverse Reactions). As familiarity with the patient's response is gained, use in anoffice setting may be acceptable.

Cardioversion has been used safely and effectively after verapamil hydrochloride injection.

CONTRAINDICATIONS

Verapamil hydrochloride injection is contraindicated in:

1. Severe hypotension or cardiogenic shock.

2. Second- or third-degree AV block (except in patients with a functioning artificial ventricular pacemaker).

3. Sick sinus syndrome (except in patients with a functioning artificial ventricular pacemaker).

4. Severe congestive heart failure (unless secondary to a supraventricular tachycardia amenable to verapamil therapy).

5. Patients receiving intravenousbeta-adrenergic blocking drugs (e.g., propranolol). Intravenousverapamil and intravenousbeta-adrenergic blocking drugs should not be administered in close proximity to each other (within a few hours), since both may have a depressant effect on myocardial contractility and AV conduction.

6. Patients with atrial flutter or atrial fibrillation and an accessory bypass tract (e.g., Wolff- Parkinson-White, Lown-Ganong-Levine syndromes) are at risk to develop ventricular tachyarrhythmia including ventricular fibrillation if verapamil is administered. Therefore, the use of verapamil in these patients is contraindicated.

7. Ventricular tachycardia: Administration of intravenous verapamil to patients with wide-complex ventricular tachycardia (QRS ≥ 0.12 sec) can result in marked hemodynamic deterioration and ventricular fibrillation. Proper pretherapy diagnosis and differentiation from wide-complex supraventricular tachycardia is imperative in the emergency room setting.

8. Known hypersensitivity to verapamil hydrochloride.

WARNINGS

VERAPAMIL HYDROCHLORIDE SHOULD BE GIVEN AS A SLOW INTRAVENOUS INJECTION OVER AT LEAST A TWO-MINUTE PERIOD OF TIME (see DOSAGE AND ADMINISTRATION).

Hypotension:Verapamil hydrochloride injection often produces a decrease in blood pressure below baseline levels that is usually transient and asymptomatic but may result in dizziness. Systolic pressure less than 90 mm Hg and/or diastolic pressure less than 60 mm Hg was seen in 5% to 10% of patients in controlled U.S. trials in supraventricular tachycardia and in about 10% of the patients with atrial flutter/fibrillation. The incidence of symptomatic hypotension observed in studies conducted in the U.S. was approximately 1.5%. Three of the five symptomatic patients required intravenous pharmacologic treatment (norepinephrine bitartrate, metaraminol bitartrate, or 10% calcium gluconate). All recovered without sequelae.

Extreme Bradycardia/Asystole:Verapamil hydrochloride affects the AV and SA nodes and rarely may produce second- or third-degree AV block, bradycardia, and, in extreme cases, asystole. This is more likely to occur in patients with a sick sinus syndrome (SA nodal disease), which is more common in older patients. Bradycardia associated with sick sinus syndrome was reported in 0.3% of the patients treated in controlled double-blind trials in the U.S. The total incidence of bradycardia (ventricular rate less than 60 beats/min) was 1.2% in these studies. Asystole in patients other than those with sick sinus syndrome is usually of short duration (few seconds or less), with spontaneous return to AV nodal or normal sinus rhythm. If this does not occur promptly, appropriate treatment should be initiated immediately. (See ADVERSE REACTIONSand Suggested Treatment of Acute Cardiovascular Adverse Reactions.)

Heart Failure:When heart failure is not severe or rate related, it should be controlled with digitalis glycosides and diuretics, as appropriate, before verapamil is used. In patients with moderately severe to severe cardiac dysfunction (pulmonary wedge pressure above 20 mm Hg, ejection fraction less than 30%), acute worsening of heart failure may be seen.

Concomitant Antiarrhythmic Therapy:

Digitalis:Verapamil hydrochloride injection has been used concomitantly with digitalis preparations without the occurrence of serious adverse effects. However, since both drugs slow AV conduction, patients should be monitored for AV block or excessive bradycardia.

Procainamide:Verapamil hydrochloride injection has been administered to a small number of patients receiving oral procainamide without the occurrence of serious adverse effects.

Quinidine:Verapamil hydrochloride injection has been administered to a small number of patients receiving oral quinidine without the occurrence of serious adverse effects. However, three patients have been described in whom the combination resulted in an exaggerated hypotensive response presumably from the combined ability of both drugs to antagonize the effects of catecholamines on α-adrenergic receptors. Caution should therefore be used when employing this combination of drugs.

Beta-Adrenergic Blocking Drugs:Verapamil hydrochloride injection has been administered to patients receiving oral beta-blockers without the development of serious adverse effects. However, since both drugs may depress myocardial contractility and AV conduction, the possibility of detrimental interactions should be considered. The concomitant administration of intravenousbeta-blockers and intravenousverapamil has resulted in serious adverse reactions (see CONTRAINDICATIONS), especially in patients with severe cardiomyopathy, congestive heart failure, or recent myocardial infarction.

Disopyramide:Until data on possible interactions between verapamil and all forms of disopyramide phosphate are obtained, disopyramide should not be administered within 48 hours before or 24 hours after verapamil administration.

Flecainide:A study in healthy volunteers showed that the concomitant administration of flecainide and verapamil may have additive effects reducing myocardial contractility, prolonging AV conduction, and prolonging repolarization.

Heart Block:Verapamil prolongs AV conduction time. While high-degree AV block has not been observed in controlled clinical trials in the United States, a low percentage (less than 0.5%) has been reported in the world literature. Development of second- or third-degree AV block or unifascicular, bifascicular, or trifascicular bundle branch block requires reduction in subsequent doses or discontinuation of verapamil and institution of appropriate therapy, if needed. (See ADVERSE REACTIONS, Suggested Treatment of Acute Cardiovascular Adverse Reactions.)

Hepatic and Renal Failure:Significant hepatic and renal failure should not increase the effects of a single intravenous dose of verapamil hydrochloride but may prolong its duration. Repeated injections of verapamil hydrochloride injection in such patients may lead to accumulation and an excessive pharmacologic effect of the drug. There is no experience to guide use of multiple doses in such patients, and this generally should be avoided. If repeated injections are essential, blood pressure and PR interval should be closely monitored and smaller repeat doses should be utilized.

Verapamil cannot be removed by hemodialysis.

Premature Ventricular Contractions:During conversion to normal sinus rhythm, or marked reduction in ventricular rate, a few benign complexes of unusual appearance (sometimes resembling premature ventricular contractions) may be seen after treatment with verapamil hydrochloride. Similar complexes are seen during spontaneous conversion of supraventricular tachycardias, after D.C.-cardioversion and other pharmacologic therapy. These complexes appear to have no clinical significance.

Duchenne's Muscular Dystrophy:Verapamil hydrochloride injection can precipitate respiratory muscle failure in these patients and should, therefore, be used with caution.

Increased Intracranial Pressure:Verapamil hydrochloride injection has been seen to increase intracranial pressure in patients with supratentorial tumors at the time of anesthesia induction. Caution should be taken and appropriate monitoring performed.

PRECAUTIONS

Drug Interactions:

(See WARNINGS: Concomitant Antiarrhythmic Therapy .) Verapamil hydrochloride injection has been used concomitantly with other cardioactive drugs (especially digitalis) without evidence of serious negative drug interactions. In rare instances, including when patients with severe cardiomyopathy, congestive heart failure, or recent myocardial infarction were given intravenousbeta-adrenergic blocking agents or disopyramide concomitantly with intravenousverapamil, serious adverse effects have occurred. Concomitant use of verapamil hydrochloride with β-adrenergic blockers may result in an exaggerated hypotensive response. Such an effect was observed in one study, following the concomitant administration of verapamil and prazosin. It may be necessary to decrease the dose of verapamil and/or dose of the neuromuscular blocking agent when the drugs are used concomitantly. As verapamil is highly bound to plasma proteins, it should be administered with caution to patients receiving other highly protein-bound drugs.

Other

Cimetidine:The interaction between cimetidine and chronically administered verapamil has not been studied. In acute studies of healthy volunteers, clearance of verapamil was either reduced or unchanged.

Lithium:Increased sensitivity to the effects of lithium (neurotoxicity) has been reported during concomitant verapamil-lithium therapy with either no change or an increase in serum lithium levels. The addition of verapamil, however, has also resulted in the lowering of serum lithium levels in patients receiving chronic stable oral lithium. Patients receiving both drugs must be monitored carefully.

Carbamazepine:Verapamil therapy may increase carbamazepine concentrations during combined therapy. This may produce carbamazepine side effects such as diplopia, headache, ataxia, or dizziness.

Rifampin:Therapy with rifampin may markedly reduce oral verapamil bioavailability.

Phenobarbital:Phenobarbital therapy may increase verapamil clearance.

Cyclosporin:Verapamil therapy may increase serum levels of cyclosporin.

Inhalation Anesthetics:Animal experiments have shown that inhalation anesthetics depress cardiovascular activity by decreasing the inward movement of calcium ions. When used concomitantly, inhalation anesthetics and calcium antagonists (such as verapamil) should be titrated carefully to avoid excessive cardiovascular depression.

Neuromuscular Blocking Agents:Clinical data and animal studies suggest that verapamil may potentiate the activity of depolarizing and nondepolarizing neuromuscular blocking agents. It may be necessary to decrease the dose of verapamil and/or the dose of the neuromuscular blocking agent when the drugs are used concomitantly.

Dantrolene:Two animal studies suggest concomitant intravenous use of verapamil and dantrolene sodium may result in cardiovascular collapse. There has been one report of hyperkalemia and myocardial depression following the coadministration of oral verapamil and intravenous dantrolene.

Pregnancy:

Teratogenic Effects:Reproduction studies have been performed in rabbits and rats at oral verapamil doses up to 1.5 (15 mg/kg/day) and 6 (60 mg/kg/day) times the human oral daily dose, respectively, and have revealed no evidence of teratogenicity. In the rat, this multiple of the human dose was embryocidal and retarded fetal growth and development, probably because of adverse maternal effects reflected in reduced weight gains of the dams. This oral dose has also been shown to cause hypotension in rats. There are, however, no adequate and well-controlled studies in pregnant women. Because animal reproduction studies are not always predictive of human response, this drug should be used during pregnancy only if clearly needed.

Labor and Delivery:

There have been few controlled studies to determine whether the use of verapamil during labor or delivery has immediate or delayed adverse effects on the fetus, or whether it prolongs the duration of labor or increases the need for forceps delivery or other obstetric intervention. Such adverse experiences have not been reported in the literature, despite a long history of use of verapamil hydrochloride injection in Europe in the treatment of cardiac side effects of beta-adrenergic agonist agents used to treat premature labor.

Nursing Mothers:

Verapamil crosses the placental barrier and can be detected in umbilical vein blood at delivery. Also, verapamil is excreted in human milk. Because of the potential for adverse reactions in nursing infants from verapamil, nursing should be discontinued while verapamil is administered.

Pediatric Use:

Controlled studies with verapamil have not been conducted in pediatric patients, but uncontrolled experience with intravenous administration in more than 250 patients, about half under 12 months of age and about 25% newborn, indicates that results of treatment are similar to those in adults. In rare instances, however, severe hemodynamic side effects − some of them fatal − have occurred following the intravenous administration of verapamil to neonates and infants. Caution should therefore be used when administering verapamil to this group of pediatric patients.The most commonly used single doses in patients up to 12 months of age have ranged from 0.1 to 0.2 mg/kg of body weight, while in patients aged 1 to 15 years, the most commonly used single doses ranged from 0.1 to 0.3 mg/kg of body weight. Most of the patients received the lower dose of 0.1 mg/kg once, but in some cases, the dose was repeated once or twice every 10 to 30 minutes.

ADVERSE REACTIONS

The following reactions were reported with verapamil hydrochloride injection used in controlled U.S. clinical trials involving 324 patients:

Cardiovascular:Symptomatic hypotension (1.5%); bradycardia (1.2%); severe tachycardia (1.0%). The worldwide experience in open clinical trials in more than 7,900 patients was similar.

Central Nervous System Effects:Dizziness (1.2%); headache (1.2%). Occasional cases of seizures during verapamil injection have been reported.

Gastrointestinal:Nausea (0.9%); abdominal discomfort (0.6%).

In rare cases of hypersensitive patients, broncho/laryngeal spasm accompanied by itch and urticaria has been reported.

The following reactions have been reported at low frequency: emotional depression, rotary nystagmus, sleepiness, vertigo, muscle fatigue, diaphoresis, and respiratory failure.

Suggested Treatment of Acute Cardiovascular Adverse Reactions*
The frequency of these adverse reactions was quite low, and experience with their treatment has been limited.
Adverse Reaction | Proven Effective Treatment | Supportive Treatment
1.Symptomatic hypotension requiring treatment | Dopamine intravenous Calcium chloride intravenous Norepinephrine bitartrate Intravenous Metaraminol bitartrate intravenous Isoproterenol HCl intravenous | Intravenous fluids Trendelenburg position
2. Bradycardia, AV block, Asystole | Isoproterenol HCl intravenous Calcium chloride intravenous Norepinephrine bitartrate intravenous Atropine intravenous Cardiac pacing | Intravenous fluids (slow drip)
3. Rapid ventricular rate (due to antegrade conduction in flutter/fibrillation with W-P-W or L-G-L syndromes) | DC-cardioversion (high energy may be required) Procainamide intravenous Lidocaine intravenous | Intravenous fluids (slow drip)

*Actual treatment and dosage should depend on the severity of the clinical situation and the judgment and experience of the treating physician.

To report SUSPECTED ADVERSE REACTIONS, contact Lifestar Pharma LLC at 1-888-995-4337 or FDA at 1-800-FDA-1088 or www.fda.gov/medwatch.

OVERDOSAGE

Treatment of overdosage should be supportive and individualized. Beta-adrenergic stimulation and/or parenteral administration of calcium injections may increase calcium ion flux across the slow channel, and have been effectively used in treatment of deliberate overdosage with oral verapamil hydrochloride. Verapamil cannot be removed by hemodialysis.

Clinically significant hypotensive reactions or high-degree AV block should be treated with vasopressor agents or cardiac pacing, respectively. Asystole should be handled by the usual measures including isoproterenol hydrochloride, other vasopressor agents, or cardiopulmonary resuscitation (see ADVERSE REACTIONS: Suggested Treatment of Acute Cardiovascular Adverse Reactions).

DOSAGE AND ADMINISTRATION

FOR INTRAVENOUS USE ONLY. VERAPAMIL HYDROCHLORIDE INJECTION SHOULD BE GIVEN AS A SLOW INTRAVENOUS INJECTION OVER AT LEAST A TWO-MINUTE PERIOD OF TIME UNDER CONTINUOUS ELECTROCARDIOGRAPHIC (ECG) AND BLOOD PRESSURE MONITORING.The recommended intravenous doses of verapamil hydrochloride injection are as follows:

Adult:

Initial dose− 5 to 10 mg (0.075 to 0.15 mg/kg body weight) given as an intravenous bolus over at least 2 minutes.

Repeat dose− 10 mg (0.15 mg/kg body weight) 30 minutes after the first dose if the initial response is not adequate. An optimal interval for subsequent intravenous doses has not been determined, and should be individualized for each patient.

Older patients− The dose should be administered over at least 3 minutes to minimize the risk of untoward drug effects.

Pediatric:

Initial dose:

0 to 1 year:0.1 to 0.2 mg/kg body weight (usual single dose range: 0.75 to 2 mg) should be administered as an intravenous bolus over at least 2 minutes under continuous ECG monitoring.

1 to 15 years:0.1 to 0.3 mg/kg body weight (usual single dose range: 2 to 5 mg) should be administered as an intravenous bolus over at least 2 minutes. Do not exceed 5 mg.

Repeat dose:

0 to 1 year:0.1 to 0.2 mg/kg body weight (usual single dose range: 0.75 to 2 mg) 30 minutes after the first dose if the initial response is not adequate (under continuous ECG monitoring). An optimal interval for subsequent intravenous doses has not been determined, and should be individualized for each patient.

1 to 15 years:0.1 to 0.3 mg/kg body weight (usual single dose range: 2 to 5 mg) 30 minutes after the first dose if the initial response is not adequate. Do not exceed 10 mg as a single dose.An optimal interval for subsequent intravenous doses has not been determined, and should be individualized for each patient.

Note:Parenteral drug products should be inspected visually for particulate matter and discoloration prior to administration, whenever solution and container permit. Use only if solution is clear and vial seal is intact. Unused amount of solution should be discarded immediately following withdrawal of any portion of contents.

For stability reasons this product is not recommended for dilution with Sodium Lactate Injection, USP in polyvinyl chloride bags. Verapamil is physically compatible and chemically stable for at least 24 hours at 25°C protected from light in most common large volume parenteral solutions. Admixing verapamil hydrochloride injection with albumin, amphotericin B, hydralazine hydrochloride and trimethoprim with sulfamethoxazole should be avoided. Verapamil hydrochloride injection will precipitate in any solution with a pH above 6.0.

HOW SUPPLIED

Verapamil Hydrochloride Injection, USP 2.5 mg/mL is a clear, colourless solution and supplied in single-dose container as follows:

NDC 84549-605-25 - Single-dose vial 2 mL (2.5mg/mL)

Store at 20º to 25°C (68º to 77°F). [See USP Controlled Room Temperature.]

Protect from light by retaining in package until ready to use.

Made in India